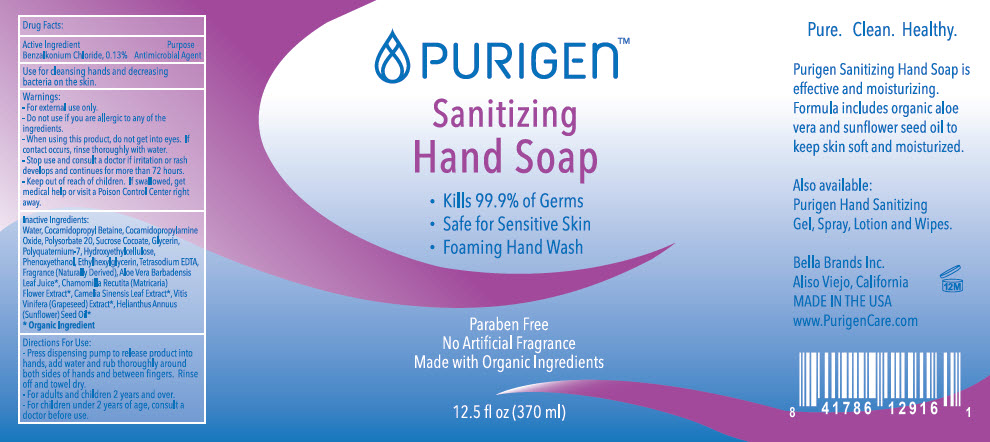 DRUG LABEL: Sanitizing Hand
NDC: 80994-004 | Form: SOAP
Manufacturer: BELLA BRANDS INC
Category: otc | Type: HUMAN OTC DRUG LABEL
Date: 20201118

ACTIVE INGREDIENTS: BENZALKONIUM CHLORIDE 1.3 mg/1 mL
INACTIVE INGREDIENTS: Water; Cocamidopropyl Betaine; Cocamidopropylamine Oxide; Polysorbate 20; Sucrose Cocoate; Glycerin; POLYQUATERNIUM-7 (70/30 ACRYLAMIDE/DADMAC; 1600000 MW); Hydroxyethyl Cellulose, Unspecified; Phenoxyethanol; Ethylhexylglycerin; Edetate Sodium; Chamomile; Green Tea Leaf; Vitis Vinifera Seed; Sunflower Oil

Sanitizing Hand

Drug Facts:

Active Ingredient

Benzalkonium Chloride, 0.13%

Purpose

Antimicrobial Agent

Use

for cleansing hands and decreasing bacteria on the skin.

Warnings

- For external use only.

- Do not use if you are allergic to any of the ingredients.

- When using this product, do not get into eyes. If contact occurs, rinse thoroughly with water.

- Stop use and consult a doctor if irritation or rash develops and continues for more than 72 hours.

- Keep out of reach of children. If swallowed, get medical help or visit a Poison Control Center right away.

Inactive Ingredients

Water, Cocamidopropyl Betaine, Cocamidopropylamine Oxide, Polysorbate 20, Sucrose Cocoate, Glycerin, Polyquaternium-7, Hydroxyethylcellulose, Phenoxyethanol, Ethylhexylglycerin, Tetrasodium EDTA, Fragrance (Naturally Derived), Aloe Vera Barbadensis Leaf Juice [Organic Ingredient] , Chamomilla Recutita (Matricaria) Flower Extract, Camelia Sinensis Leaf Extract, Vitis Vinifera (Grapeseed) Extract, Helianthus Annuus (Sunflower) Seed Oil

Directions For Use

- Press dispensing pump to release product into hands, add water and rub thoroughly around both sides of hands and between fingers. Rinse off and towel dry.

- For adults and children 2 years and over.

- For children under 2 years of age, consult a doctor before use.

PRINCIPAL DISPLAY PANEL - 370 ml Bottle Label

PURIGEN™

Sanitizing
Hand Soap

- Kills 99.9% of Germs
- Safe for Sensitive Skin
- Foaming Hand Wash

Paraben Free
No Artificial Fragrance
Made with Organic Ingredients

12.5 fl oz (370 ml)